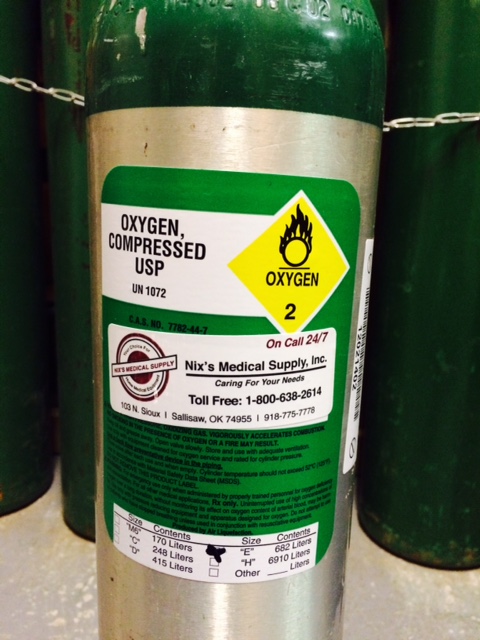 DRUG LABEL: Oxygen
NDC: 64201-001 | Form: GAS
Manufacturer: Nix's Medical Supply, Inc.
Category: prescription | Type: HUMAN PRESCRIPTION DRUG LABEL
Date: 20141204

ACTIVE INGREDIENTS: OXYGEN .99 L/1 L

Medical Oxygen